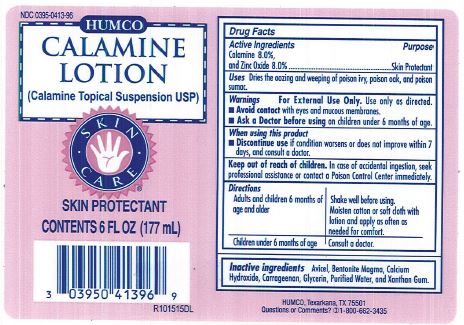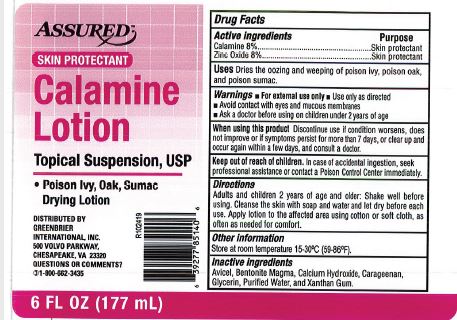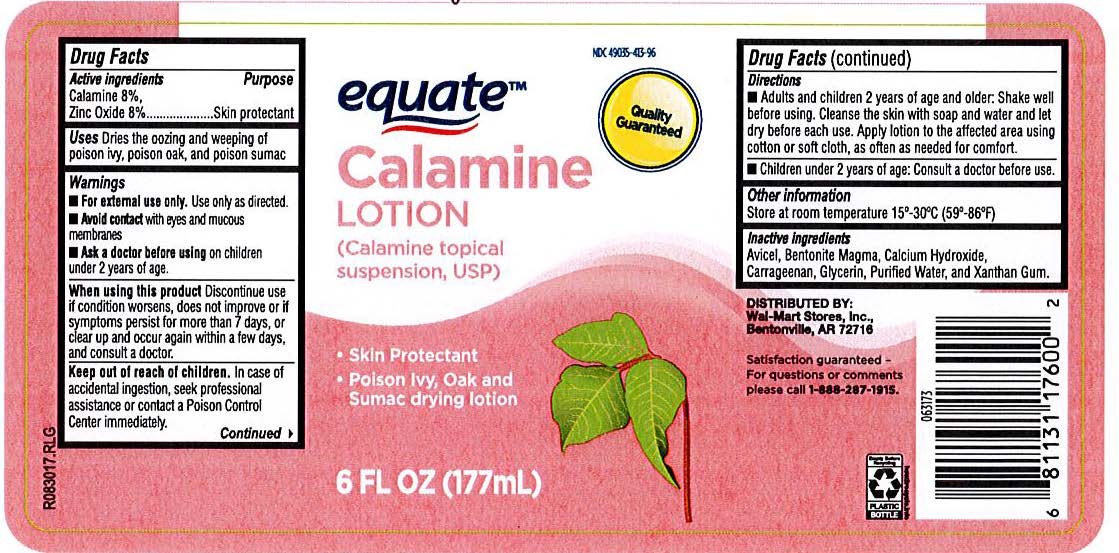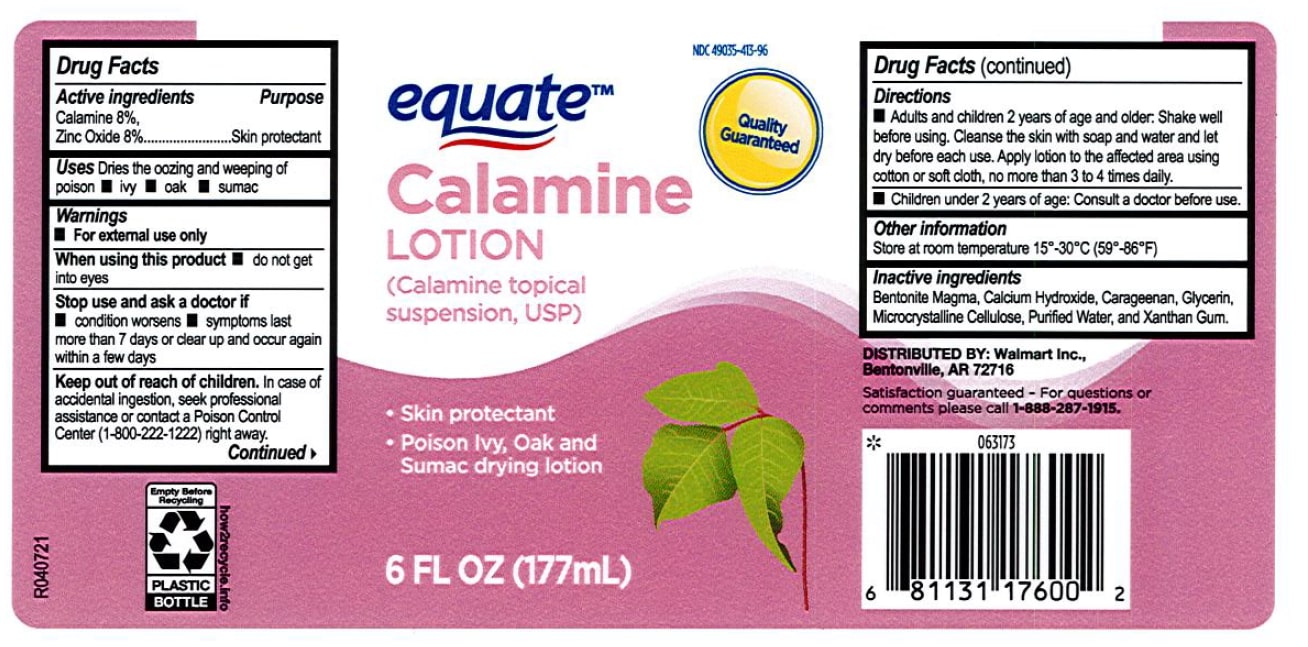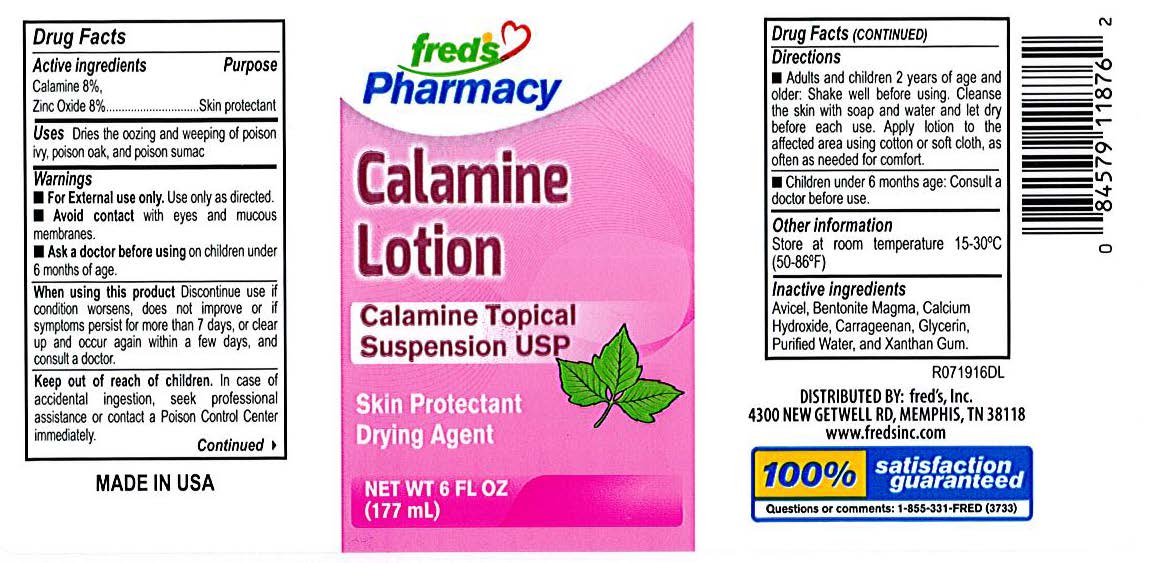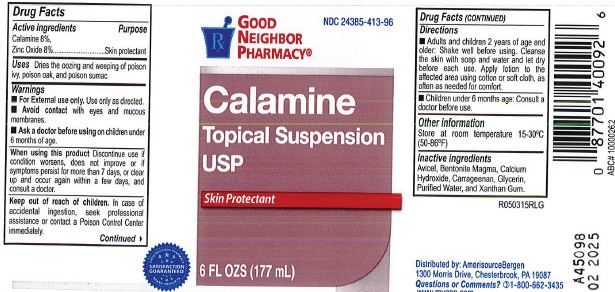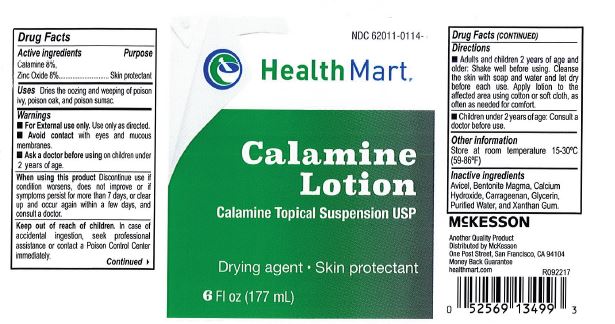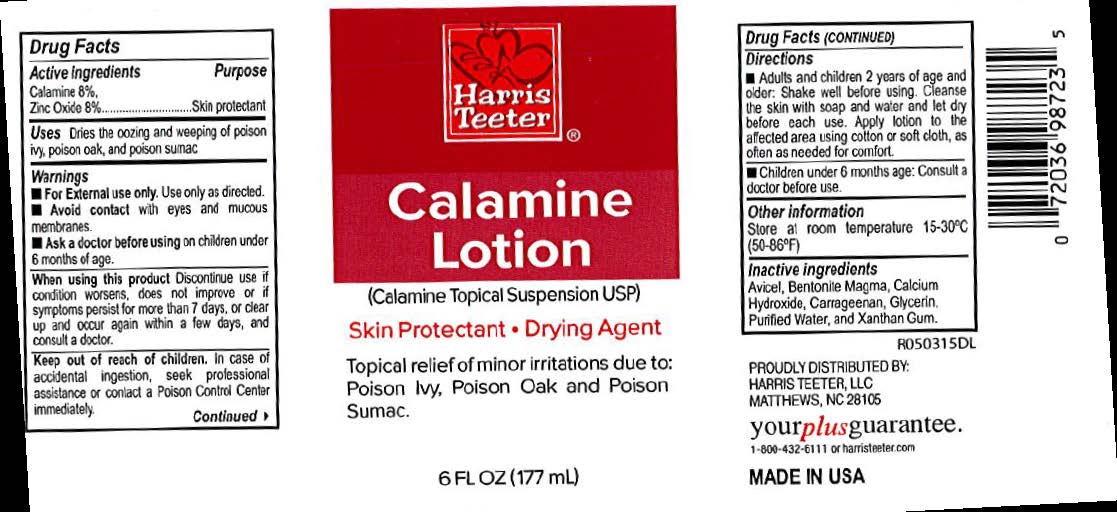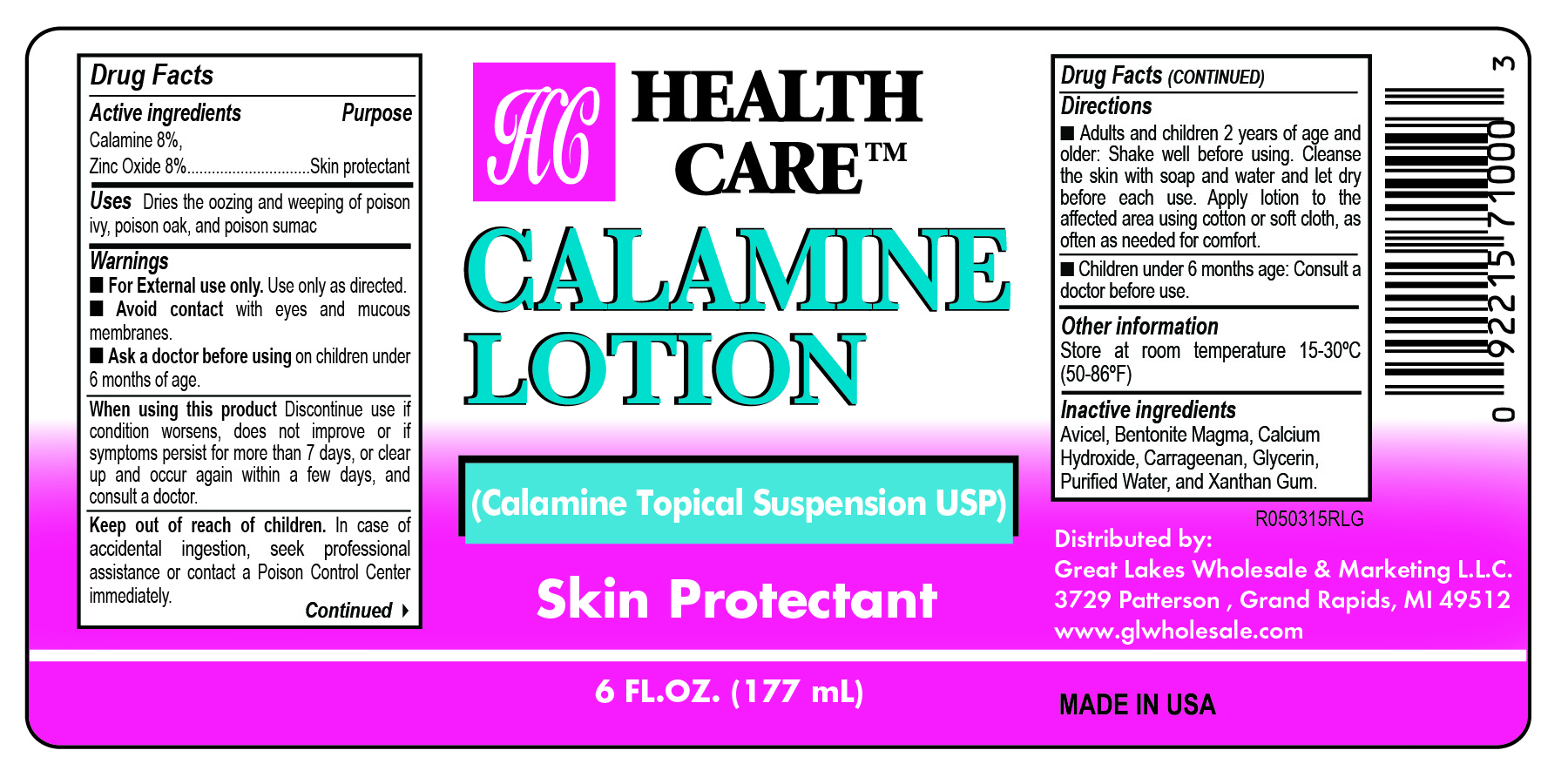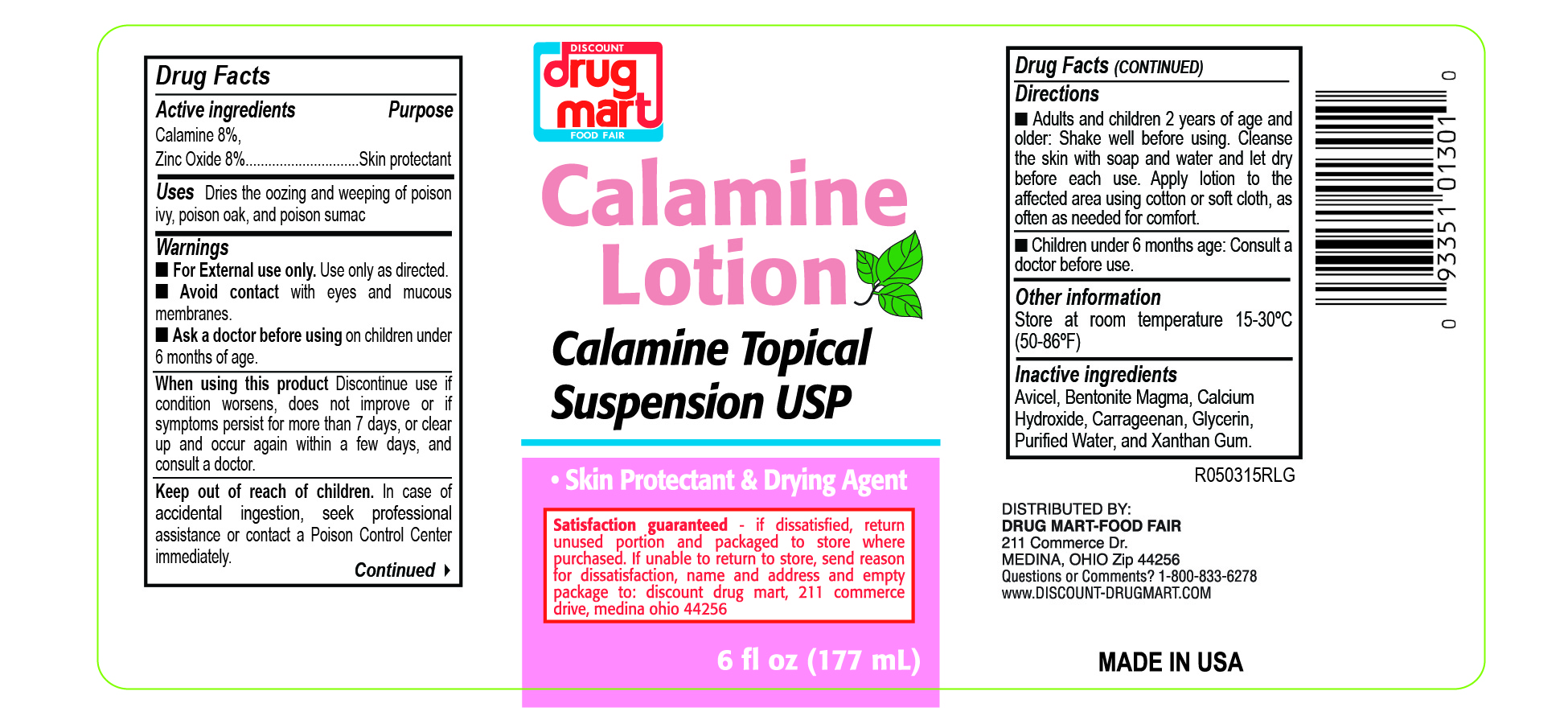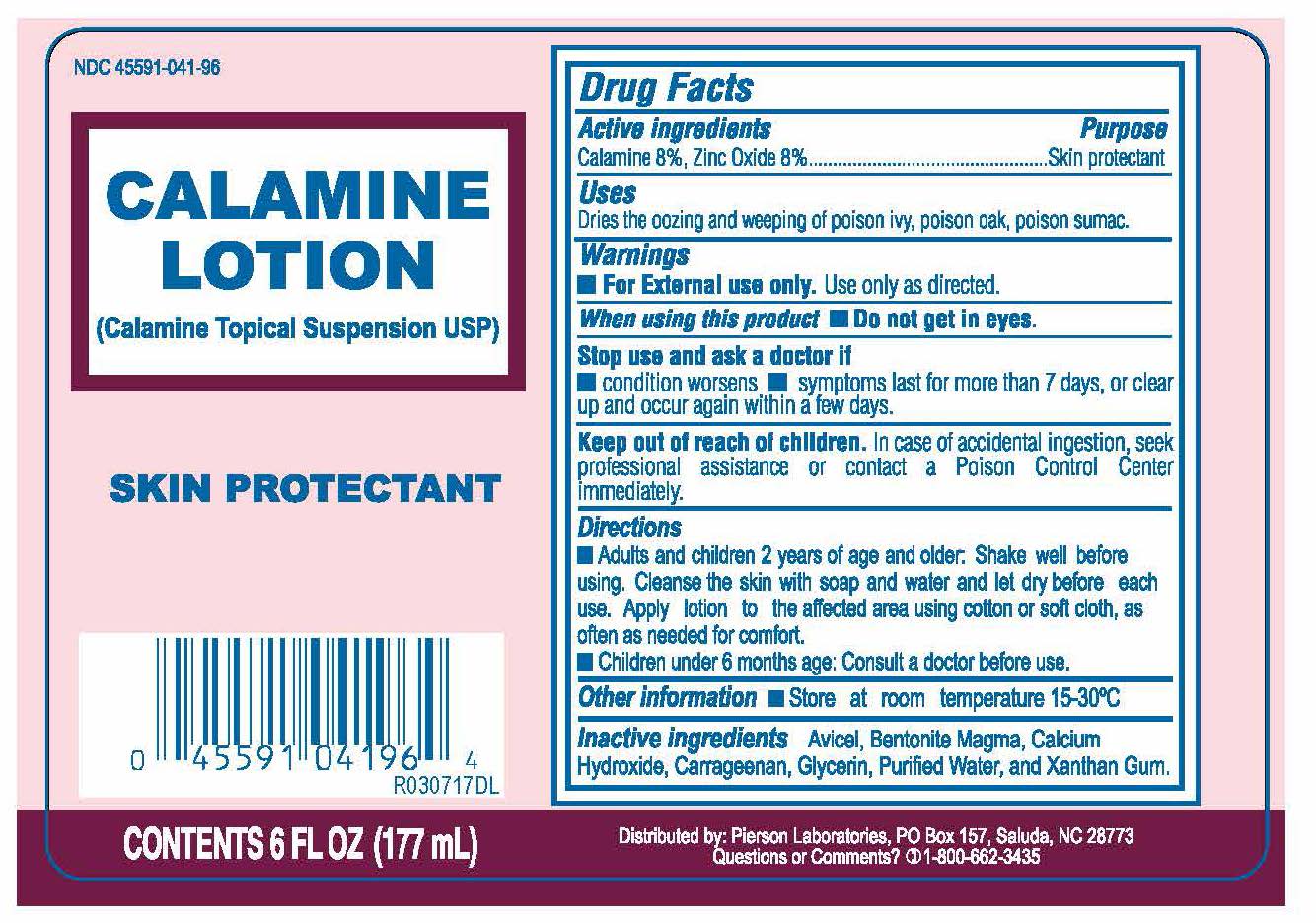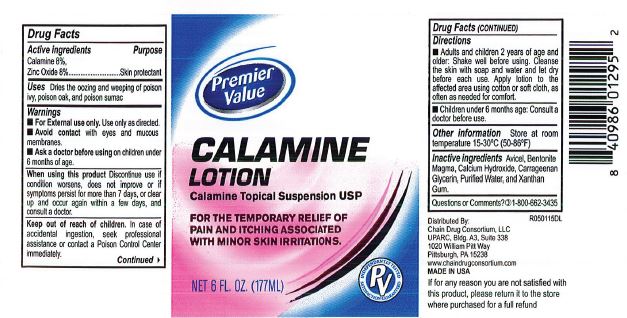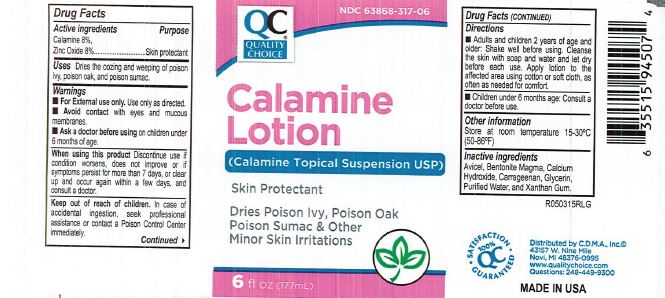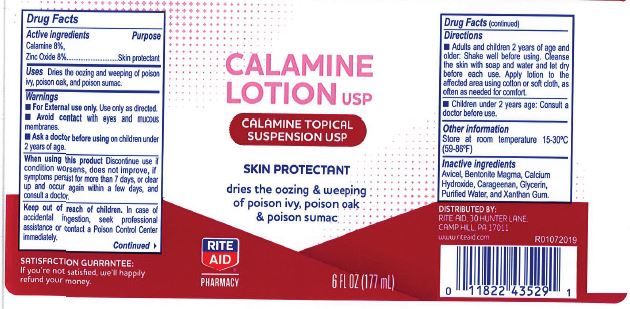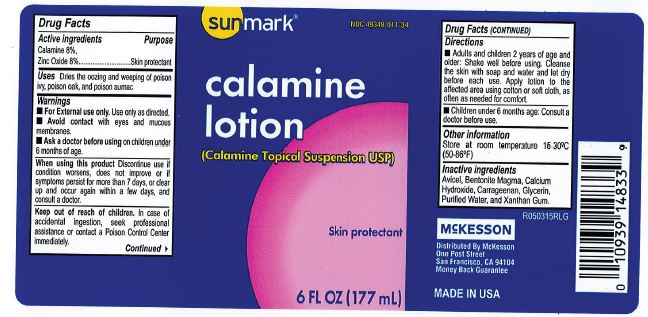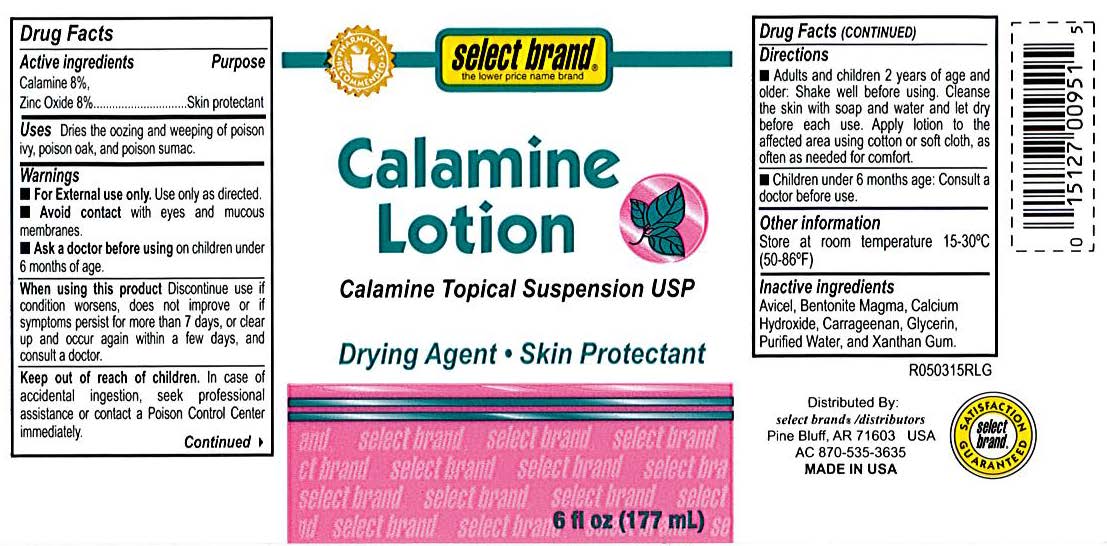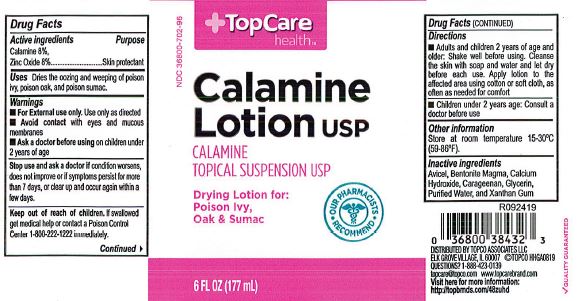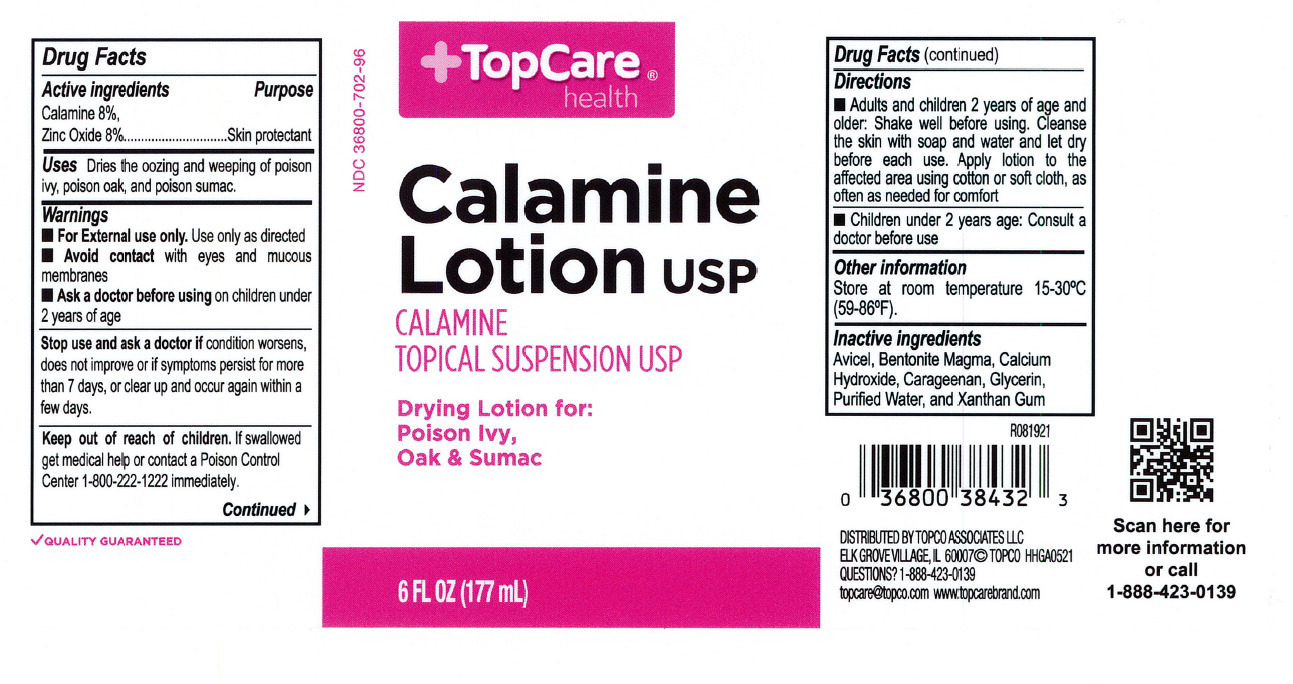 DRUG LABEL: Calamine
NDC: 82645-900 | Form: LOTION
Manufacturer: Pharma Nobis, LLC
Category: otc | Type: HUMAN OTC DRUG LABEL
Date: 20231222

ACTIVE INGREDIENTS: ZINC OXIDE 160 mg/1 mL
INACTIVE INGREDIENTS: CARRAGEENAN; XANTHAN GUM; CALCIUM HYDROXIDE; GLYCERIN; WATER; MICROCRYSTALLINE CELLULOSE; BENTONITE

Private Label Calamine Lotion

Drug Facts

Active Ingredients

Calamine 8% and Zinc Oxide 8%

Purpose

Skin protectant

Uses

dries the oozing and weeping o poison ivy, poison oak, and poison sumac.

Warnings

For external use only. Use only as directed.

Avoid contact with eyes and mucous membranes.

Ask a doctor before using on chilren 6 months of age.

When using this product

Discontinue use if condition worsens or does not improve within 7 days and consult a doctor.

Keep out of reach of children

In case of accidental ingestion, seek professional assistance or contact a Poison Control center immediately.

Directions

Adults and chidren 2 years of age and older: shake well before using. Cleanse the skin with soap and water and let it dry befroe each use. Apply lotion to the affected area using a cotton or soft cloth, as often as needed for comfort.

Children under 2 years of age: Consult a doctor before use

Directions

Children under 2 years of age: Consult a doctor before use (12/2021)

Other information

Store at room temperature 13-30C (50-86F)

Inactive ingredients

Bentonite magma, calcium hydroxide, glycerin, purified water.